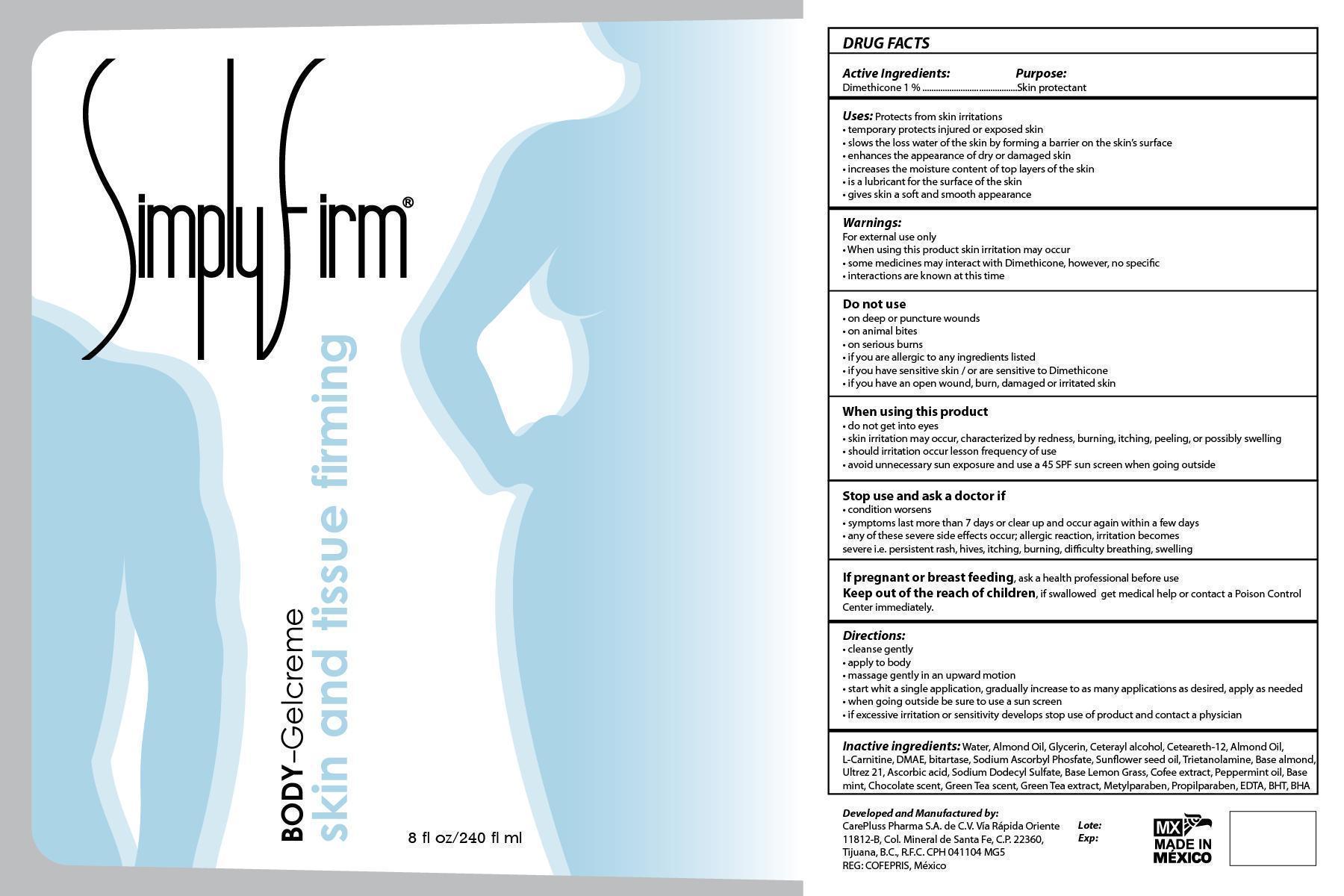 DRUG LABEL: Simply Firm - Body
NDC: 51439-003 | Form: GEL
Manufacturer: CarePluss Pharma S.A. de C.V.
Category: otc | Type: HUMAN OTC DRUG LABEL
Date: 20130423

ACTIVE INGREDIENTS: Dimethicone .0024 mg/.024 mg
INACTIVE INGREDIENTS: Water; Glycerin; CETYL ALCOHOL; CETEARETH-12; ALMOND OIL; LEVOCARNITINE; DEANOL; SODIUM ASCORBYL PHOSPHATE; SUNFLOWER OIL; CARBOMER COPOLYMER TYPE A (ALLYL PENTAERYTHRITOL CROSSLINKED); WEST INDIAN LEMONGRASS OIL; TROLAMINE; SODIUM DODECYLBENZENESULFONATE; ASCORBIC ACID; PEPPERMINT OIL; MINT; ALMOND; GREEN TEA LEAF; EDETIC ACID; METHYLPARABEN; PROPYLPARABEN; BUTYLATED HYDROXYTOLUENE; BUTYLATED HYDROXYANISOLE

Active Ingredients...........Purpose

Dimethicone 1%.............Skin Protectant

PURPOSE

Uses: protects from minor skin irritations.

- temporarily protects injured or exposed skin
- slows the loss of water of the skin by forming a barrier on the skin's surface
- enhances the appearance of dry or damaged skin
- increases the water content of the top layers of the skin
- is a lubricant for the surface of the skin
- gives skin a soft and smooth appearance

Warnings: For external use only

- when using this product skin irritation may occur
- some medicines may interact with dimethicone, however, no specific interactions are known at this time

Do not use

- if you are allergic to any ingredients listed
- if you have sensitive skin and/or are sensitive to Dimethicone
- do not use if you are pregnant, planning to become pregnant, or breast feeding
- if you have an open wound, burn, damaged or irritaed skin

When using this product

- skin irritation may occur, characterized by redness, burning, itching, peeling, or possibly swelling
- should irritation occur lesson frequency of use
- avoid unnecessary sun exposure and use a 45 SPF sun screen when going outside

Stop use and ask a doctor if:

- condition worsens
- symptoms last more than 7 days or clear up and occur again within a few days
- any of these severe effects occur; allergic reaction, irritation becomes severe i.e. persistent rash, hives, itching, burning, difficulty breathing, swelling

Keep out of reach of children. If swallowed get medical help or contact a Poison Control Center immediately

Directions:

- cleanse gently
- apply to body
- massage into desired area using long upward strokes
- start with a single application, gradually increase to as many applications as desired
- when going outside be sure to use a 45 SPF SUN SCREEN applicable to the area
- if excessive irritation or sensitivity develops stop use of product and contact a physician

INACTIVE INGREDIENT

Other ingredients: Water, Almond Oil, Glycerin, Cetearyl alcohol, Cetearteh-12, almond Oil, L-Carnitine, DMAE, Bitartrate, Sodium Ascorbyl Fosphate,, Sunflower Seed Oil, Green Tea extract, Coffee extract, Sodium Dodecyl Sulphate, Base Lemon Grass, Pepermint Oil, Menthol, Ultrex 21, Green Tea scent, EDTA, BHT, BHA.

DOSAGE AND ADMINISTRATION

8 fl oz / 240 fl ml

PACKAGE LABEL

Simply Firm Body - Gelcreme Skin and tissue firming